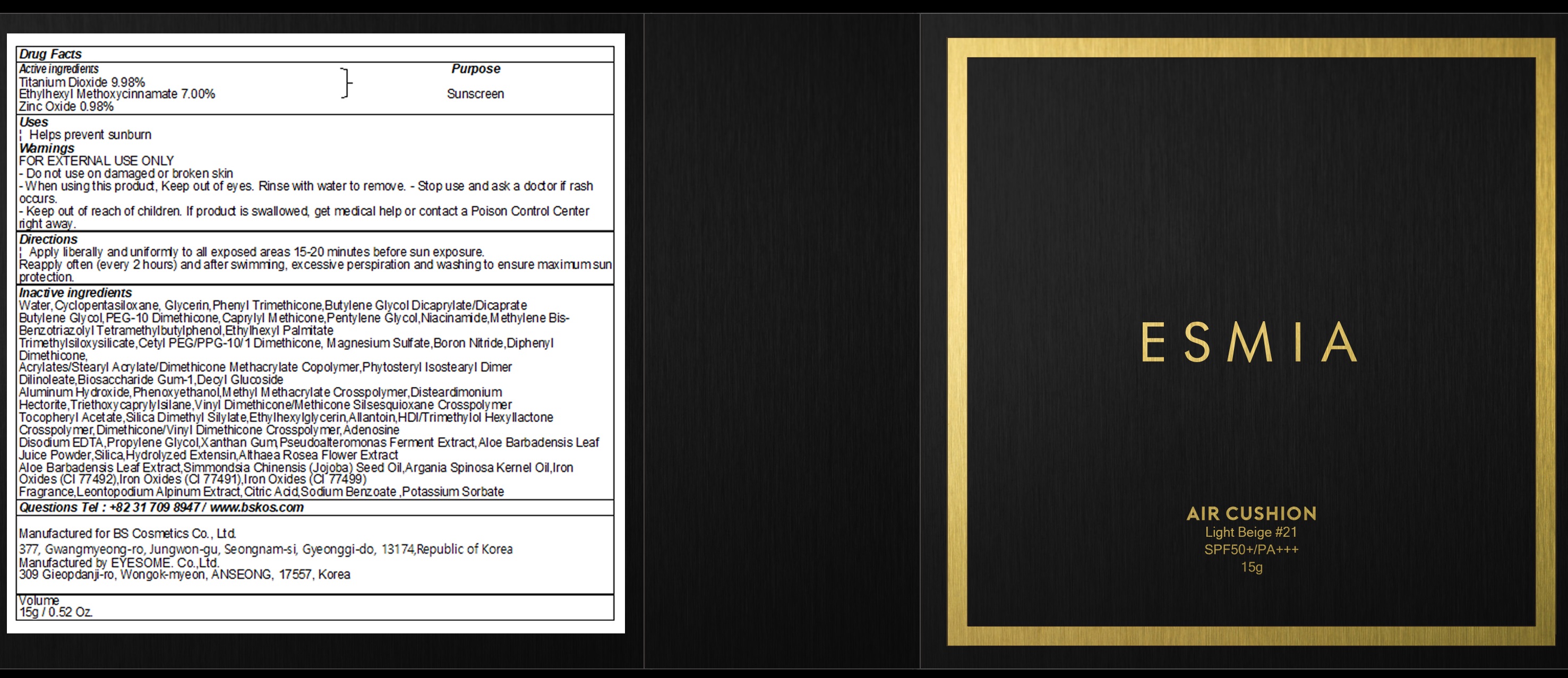 DRUG LABEL: ESMIA AIR CUSHION LIGHT BEIGE 21
NDC: 72600-190 | Form: POWDER
Manufacturer: Bs Cosmetics Co.,ltd.
Category: otc | Type: HUMAN OTC DRUG LABEL
Date: 20181019

ACTIVE INGREDIENTS: TITANIUM DIOXIDE 1.49 g/15 g; Octinoxate 1.05 g/15 g; Zinc Oxide 0.80 g/15 g
INACTIVE INGREDIENTS: Water; CYCLOMETHICONE 5

Active Ingredients

Active ingredients: Titanium Dioxide 9.98%, Ethylhexyl Methoxycinnamate 7.00%, Zinc Oxide 0.98%

INACTIVE INGREDIENT

Inactive ingredients:

Water,Cyclopentasiloxane, Glycerin,Phenyl Trimethicone,Butylene Glycol Dicaprylate/Dicaprate
Butylene Glycol,PEG-10 Dimethicone,Caprylyl Methicone,Pentylene Glycol,Niacinamide,Methylene Bis-Benzotriazolyl Tetramethylbutylphenol,Ethylhexyl Palmitate
Trimethylsiloxysilicate,Cetyl PEG/PPG-10/1 Dimethicone, Magnesium Sulfate,Boron Nitride,Diphenyl Dimethicone,
Acrylates/Stearyl Acrylate/Dimethicone Methacrylate Copolymer,Phytosteryl Isostearyl Dimer Dilinoleate,Biosaccharide Gum-1,Decyl Glucoside
Aluminum Hydroxide,Phenoxyethanol,Methyl Methacrylate Crosspolymer,Disteardimonium Hectorite,Triethoxycaprylylsilane,Vinyl Dimethicone/Methicone Silsesquioxane Crosspolymer
Tocopheryl Acetate,Silica Dimethyl Silylate,Ethylhexylglycerin,Allantoin,HDI/Trimethylol Hexyllactone Crosspolymer,Dimethicone/Vinyl Dimethicone Crosspolymer,Adenosine
Disodium EDTA,Propylene Glycol,Xanthan Gum,Pseudoalteromonas Ferment Extract,Aloe Barbadensis Leaf Juice Powder,Silica,Hydrolyzed Extensin,Althaea Rosea Flower Extract
Aloe Barbadensis Leaf Extract,Simmondsia Chinensis (Jojoba) Seed Oil,Argania Spinosa Kernel Oil,Iron Oxides (CI 77492),Iron Oxides (CI 77491),Iron Oxides (CI 77499)
Fragrance,Leontopodium Alpinum Extract,Citric Acid,Sodium Benzoate ,Potassium Sorbate

Purpose

Purpose: Sunscreen

Warnings

FOR EXTERNAL USE ONLY

- Do not use on damaged or broken skin

- When using this product, Keep out of eyes. Rinse with water to remove.

- Stop use and ask a doctor if rash occurs.

- Keep out of reach of children. If product is swallowed, get medical help or contact a Poison Control Center right away.

DESCRIPTION

Uses:

Helps prevent sunburn

Directions:

Apply liberally and uniformly to all exposed areas 15-20 minutes before sun exposure.

Reapply often (every 2 hours) and after swimming, excessive perspiration and washing to ensure maximum sun protection.